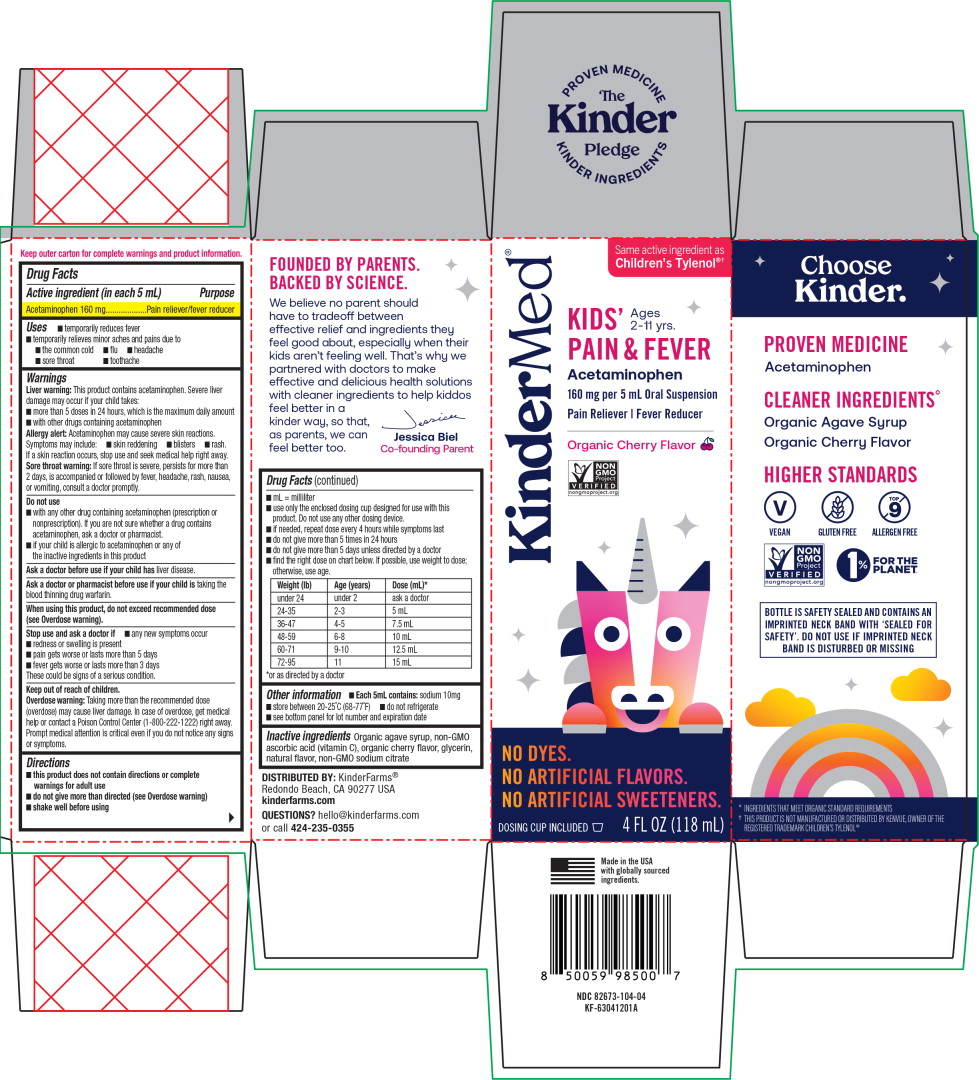 DRUG LABEL: Kids Pain and Fever
NDC: 82673-104 | Form: SUSPENSION
Manufacturer: KinderFarms, LLC
Category: otc | Type: HUMAN OTC DRUG LABEL
Date: 20250601

ACTIVE INGREDIENTS: ACETAMINOPHEN 160 mg/5 mL
INACTIVE INGREDIENTS: AGAVE TEQUILANA JUICE; ASCORBIC ACID; GLYCERIN; SODIUM CITRATE, UNSPECIFIED FORM

Drug Facts

Active ingredient (in each 5 mL)

Acetaminophen 160 mg

Purpose

Pain reliever/fever reducer

Uses

- temporarily reduces fever
- temporarily relieves minor aches and pains due to
  - the common cold
  - flu
  - headache
  - sore throat
  - toothache

Warnings

Liver warning: This product contains acetaminophen. Severe liver damage may occur if your child takes:

- more than 5 doses in 24 hours, which is the maximum daily amount
- with other drugs containing acetaminophen

Allergy alert: Acetaminophen may cause severe skin reactions.

Symptoms may include:

- skin reddening
- blisters
- rash.

If a skin reaction occurs, stop use and seek medical help right away.

Sore throat warning: If sore throat is severe, persists for more than 2 days, is accompanied or followed by fever, headache, rash, nausea, or vomiting, consult a doctor promptly.

Do not use

- with any other drug containing acetaminophen (prescription or nonprescription). If you are not sure whether a drug contains acetaminophen, ask a doctor or pharmacist.
- if your child is allergic to acetaminophen or any of the inactive ingredients in this product

Ask a doctor before use if your child has liver disease.

Ask a doctor or pharmacist before use if your child is taking the blood thinning drug warfarin.

When using this product, do not exceed recommended dose (see Overdose warning).

Stop use and ask a doctor if

- any new symptoms occur
- redness or swelling is present
- pain gets worse or lasts more than 5 days
- fever gets worse or lasts more than 3 days

These could be signs of a serious condition.

Overdose warning:

Taking more than the recommended dose (overdose) may cause liver damage. In case of overdose, get medical help or contact a Poison Control Center (1-800-222-1222) right away. Prompt medical attention is critical even if you do not notice any signs or symptoms.

Directions

- this product does not contain directions or complete warnings for adult use
- do not give more than directed (see Overdose warning)
- shake well before using
- mL = milliliter
- use only the enclosed dosing cup designed for use with this product. Do not use any other dosing device.
- if needed, repeat dose every 4 hours while symptoms last
- do not give more than 5 times in 24 hours
- do not give more than 5 days unless directed by a doctor
- find the right dose on chart below. If possible, use weight to dose; otherwise, use age.

Weight (lb) | Age (years) | Dose (mL)*
under 24 | under 2 | ask a doctor
24-35 | 2-3 | 5 mL
36-47 | 4-5 | 7.5 mL
48-59 | 6-8 | 10 mL
60-71 | 9-10 | 12.5 mL
72-95 | 11 | 15 mL
*or as directed by a doctor

Other information

- Each 5mL contains: sodium 10mg
- store between 20-25˚C (68-77˚F)
- do not refrigerate
- see bottom panel for lot number and expiration date

Inactive ingredients

Organic agave syrup, non-GMO ascorbic acid (vitamin C), organic cherry flavor, glycerin, natural flavor, non-GMO sodium citrate

DISTRIBUTED BY: KinderFarms®
Redondo Beach, CA 90277 USA
kinderfarms.com

QUESTIONS?

hello@kinderfarms.com
or call 424-235-0355

Principal Display Panel - 118 mL Carton Label

KinderMed®

Same active ingredient as
Children's Tylenol®†

Ages
2-11 yrs.

KIDS'
PAIN & FEVER
Acetaminophen

160 mg per 5 mL Oral Suspension

Pain Reliever | Fever Reducer

Organic Cherry Flavor

NON
GMO
Project

VERIFIED

nongmoproject.org

NO DYES.

NO ARTIFICIAL FLAVORS.

NO ARTIFICIAL SWEETENERS.

DOSING CUP INCLUDED

4 FL OZ (118 mL)